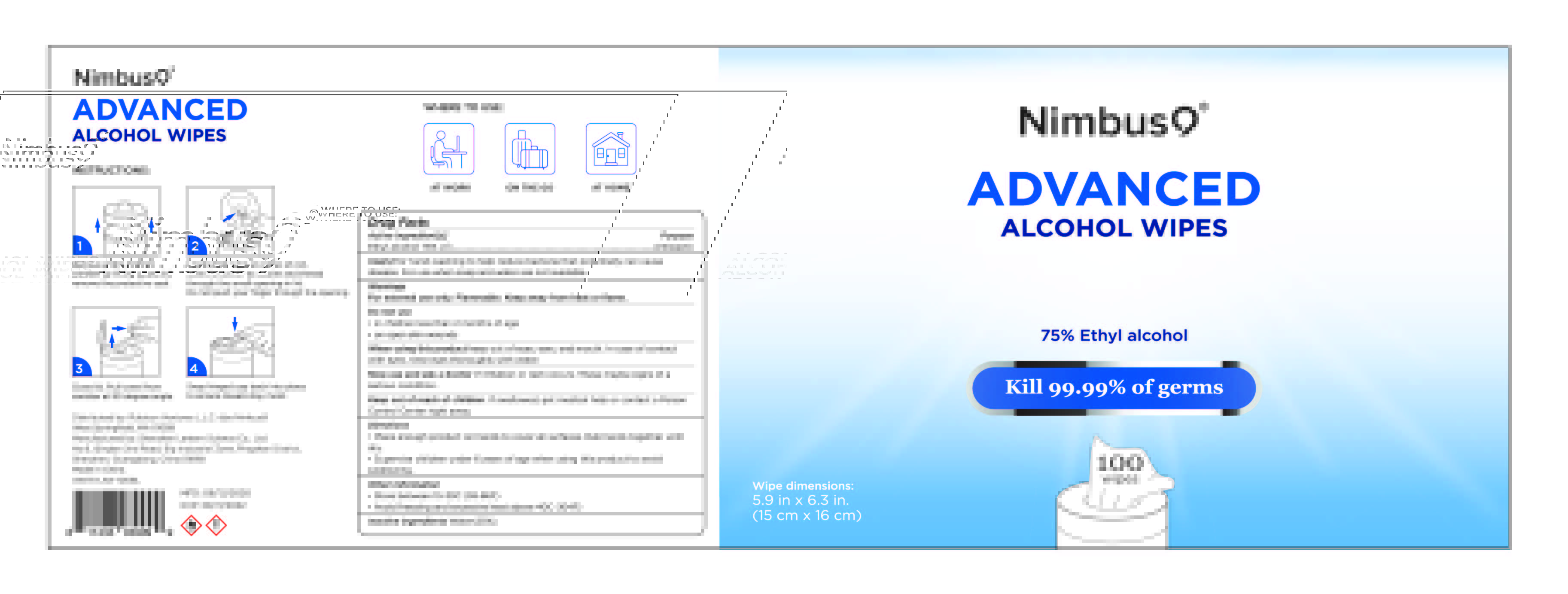 DRUG LABEL: Nimbus9 alcohol wipes

NDC: 54860-289 | Form: CLOTH
Manufacturer: Shenzhen Lantern Science Co.,Ltd.
Category: otc | Type: HUMAN OTC DRUG LABEL
Date: 20211227

ACTIVE INGREDIENTS: ALCOHOL 75 1/100 1
INACTIVE INGREDIENTS: WATER 25 1/100 1

Lantern-Nimbus9 alcohol wipes

Active ingredient

Active ingredient purpose

Ethyl alcohol 75%v/v antiseptic

Use

for hand-washing to help reduce bacteria that potentially can cause disesase.For use when soap and waterare not available.

warnings

For external use only.Flammable.Keep away from heat or flame.

Do not use

in children less than 2 months of age

on open skin wounds.

When using this product

Keep out of eyes,ears,and mouth.In case of contact with eyes,rinse eyes thoroughly with water.

Stop use and ask a doctor

if irritation or rash occurs,these maybe signs of a serious condition.

Keep out of reach of children

if swallowed,get medical help or contact a Poison Control Center right away.

Directions

Place enough product on hands to cover all surfaces and rub hands together until dry.

Supervise children under 6 years of age when using this product to avoid swallowing

Other information

Store between15-30C(59-86F)

Avoid freezing and excessive heat above 40C(104F)

Inactive ingredient

Purified Water(25%)

usage

Place enough product on hands to cover all surfaces,Rub hands together until dry.

Supervise children under 6 years of age when using this product to avoid swallowing